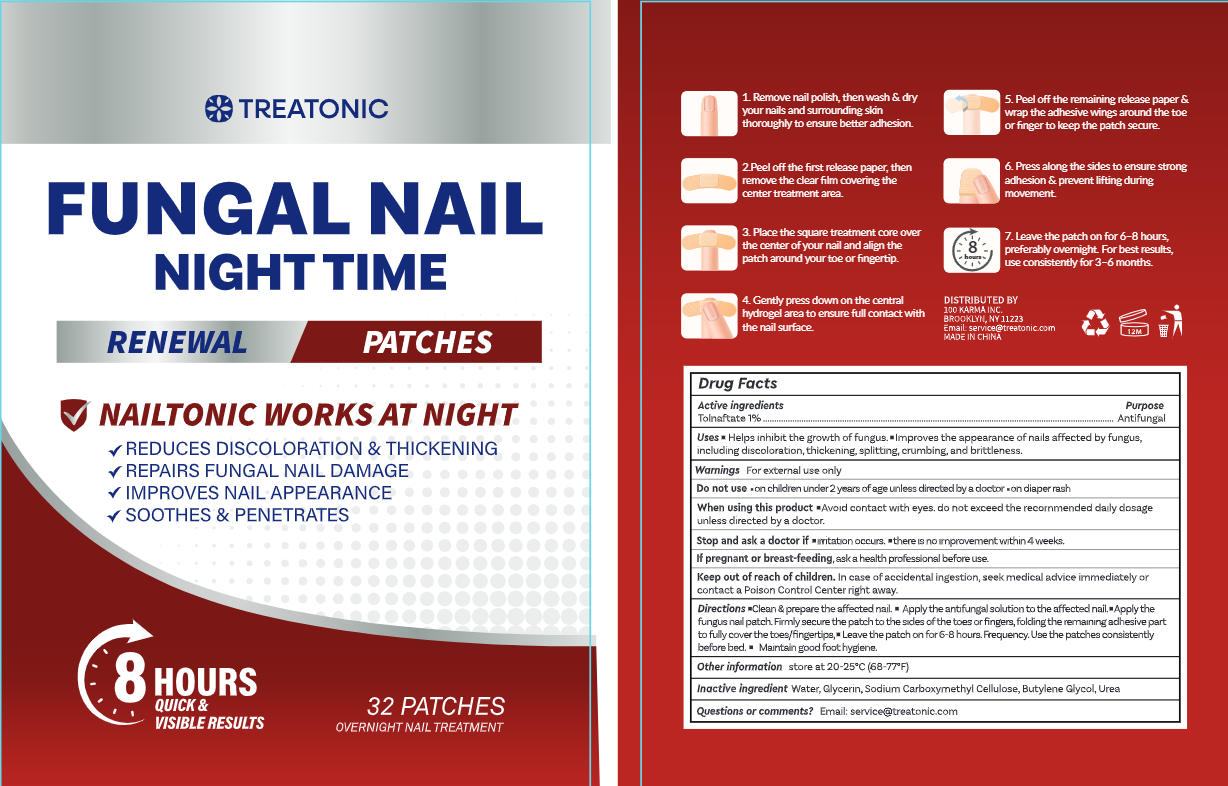 DRUG LABEL: Initial Treatonic FUNGAL NAIL RENEWAL PATCHES
NDC: 85569-013 | Form: PATCH
Manufacturer: 100 KARMA INC
Category: otc | Type: HUMAN OTC DRUG LABEL
Date: 20260302

ACTIVE INGREDIENTS: TOLNAFTATE 1 mg/100 1
INACTIVE INGREDIENTS: CARBOXYMETHYLCELLULOSE SODIUM; UREA; WATER; BUTYLENE GLYCOL; GLYCERIN

Update-85569-013-01--156

ACTIVE INGREDIENT

Tolnaftate 1%

PURPOSE

Antifungal

DOSAGE AND ADMINISTRATION

- Helps inhibit the growth of fungus.
- Improves the appearance of nails affected by fungus,including discoloration, thickening, splitting, crumbing, and brittleness.

WARNINGS

For external use only

DO NOT USE

- on children under 2years of age unless directed lby a doctor
- on dliaper rash

WHEN USING

Avoid contact with eyes. do not exceed the recommended daily dosage unless directed by a doctor.

ASK DOCTOR/PHARMACIST

- iritation occurs
- there is no improvement within 4 weeks.

PREGNANCY OR BREAST FEEDING

ask a health professional before use.

KEEP OUT OF REACH OF CHILDREN

In case of accidental ingestion, seek medical advice immediately or contact a Poison Control Center right away.

INDICATIONS AND USAGE

- Clean & prepare the affected nail,
- Applythe antifungal solution to the affected nail.
- Apply the fungus nail patch, Fimly secure the patch to the sides of the toes or fingers,folding the remaining achesive partto fully cover the toes/fingertips.
- Leave the patch on for 6-8 hours.Frequency. Use the patches consistently before bed.
- Maintain good foothygiene.

OTHER SAFETY INFORMATION

store at 20-25°C(68-77°F)

INACTIVE INGREDIENT

Water, Glycerin, Sodium Carboxymethyl Cellulose,Butylene Glycol, Urea

QUESTIONS

Email: service@treatonic.com